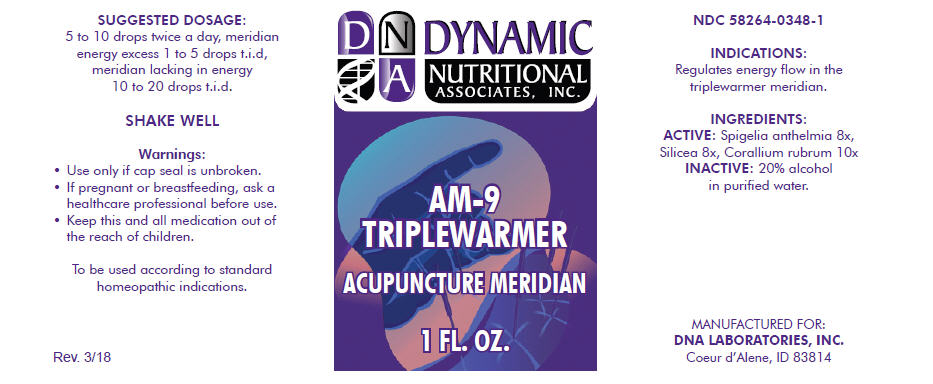 DRUG LABEL: AM-9
NDC: 58264-0348 | Form: SOLUTION
Manufacturer: DNA Labs, Inc.
Category: homeopathic | Type: HUMAN OTC DRUG LABEL
Date: 20250109

ACTIVE INGREDIENTS: SPIGELIA ANTHELMIA 8 [hp_X]/1 mL; SILICON DIOXIDE 8 [hp_X]/1 mL; CORALLIUM RUBRUM WHOLE 10 [hp_X]/1 mL
INACTIVE INGREDIENTS: ALCOHOL; WATER

AM-9

NDC 58264-0348-1

INDICATIONS

PURPOSE

Regulates energy flow in the triplewarmer meridian.

INGREDIENTS

ACTIVE

Spigelia anthelmia 8x, Silicea 8x, Corallium rubrum 10x

INACTIVE

20% alcohol in purified water.

SUGGESTED DOSAGE

5 to 10 drops twice a day, meridian energy excess 1 to 5 drops t.i.d, meridian lacking in energy 10 to 20 drops t.i.d.

STORAGE AND HANDLING

SHAKE WELL

Warnings

- Use only if cap seal is unbroken.

PREGNANCY OR BREAST FEEDING

- If pregnant or breastfeeding, ask a healthcare professional before use.

KEEP OUT OF REACH OF CHILDREN

- Keep this and all medication out of the reach of children.

To be used according to standard homeopathic indications.

PRINCIPAL DISPLAY PANEL - 1 FL. OZ. Bottle Label

DYNAMIC
NUTRITIONAL
ASSOCIATES, INC.

AM-9
TRIPLEWARMER

ACUPUNCTURE MERIDIAN

1 FL. OZ.